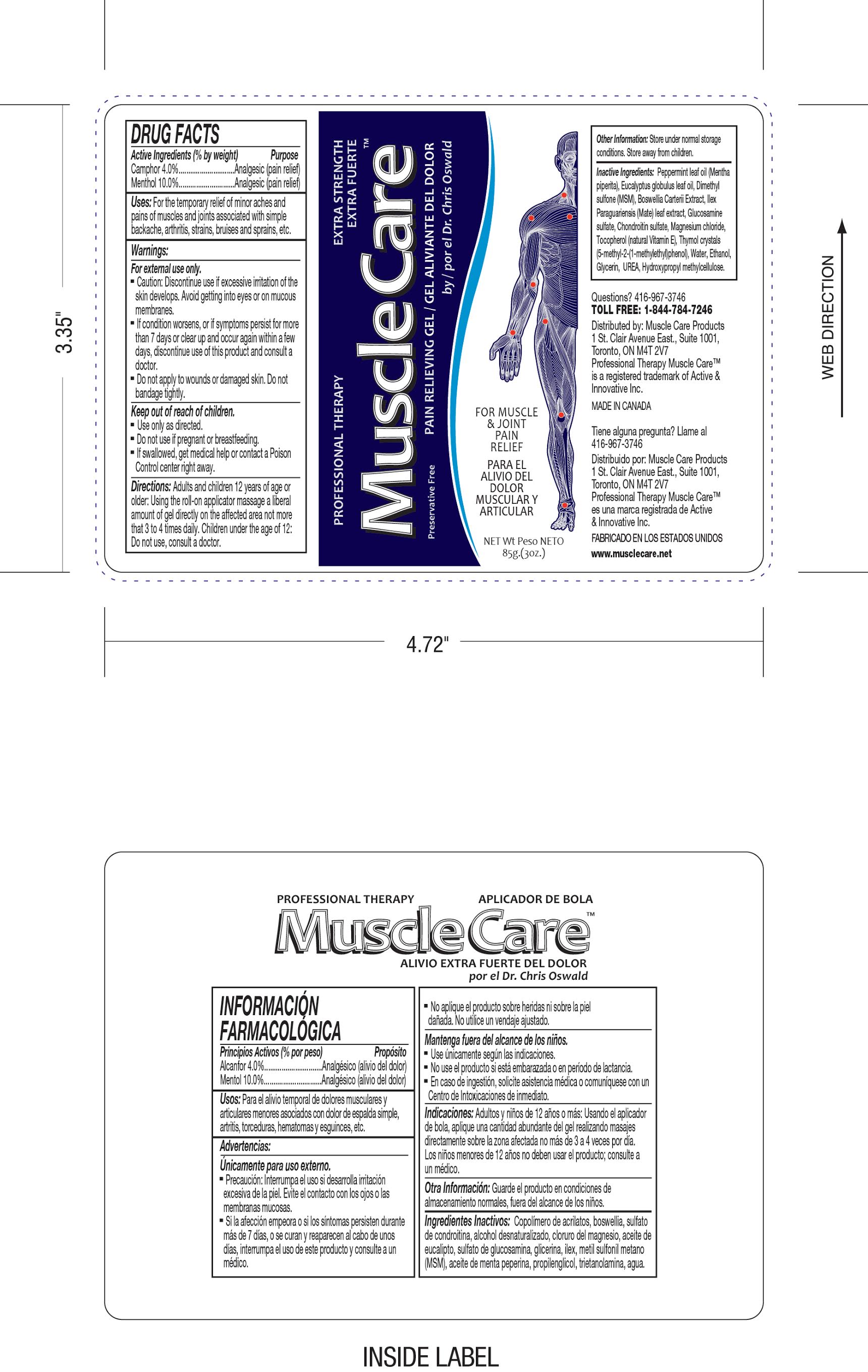 DRUG LABEL: Professional Therapy MuscleCare
NDC: 70039-200 | Form: GEL
Manufacturer: Active and Innovative Inc.
Category: otc | Type: HUMAN OTC DRUG LABEL
Date: 20210803

ACTIVE INGREDIENTS: MENTHOL 100 mg/1 g; CAMPHOR (SYNTHETIC) 40 mg/1 g
INACTIVE INGREDIENTS: EUCALYPTUS OIL; DIMETHYL SULFONE; INDIAN FRANKINCENSE; ILEX PARAGUARIENSIS LEAF; PEPPERMINT OIL; GLUCOSAMINE SULFATE; CHONDROITIN SULFATE (CHICKEN); MAGNESIUM CHLORIDE; TOCOPHEROL; THYMOL; WATER; ALCOHOL; GLYCERIN; UREA; HYPROMELLOSES

Professional Therapy MuscleCare pain relieving gel, 3 oz. roll-on

PURPOSE

For Muscle and Joint Pain Relief

ACTIVE INGREDIENTS (% BY WEIGHT) PURPOSE

Camphor 4.0%.................. Analgesic (pain relief)

Menthol 10.0%...................Analgesic (pain relief)

USES:

For the temporary relief of minor aches and pains of muscles and joints associated with simple backache, arthritis, strains, bruises, and sprains, etc.

WARNINGS:

For external use only.

Caution: Discontinue use if excessive irritation of the skin develops. Avoid getting into eyes or on mucous membranes.

If condition worsens, or if symptoms persist for more than 7 days or clear up and occur again within a few days, discontinue use of this product and consult a doctor.

Do not apply to wounds or damaged skin. Do not bandage tightly.

KEEP OUT OF REACH OF CHILDREN:

Use only as directed.

Do not use if pregnant or breastfeeding.

If swallowed, get medical help or contact a Poison Control center right away.

DOSAGE AND ADMINISTRATION

Directions: Adults and children 12 years of age or older: Using the roll-on applicator massage a liberal amount of gel directly onto the affected area not more than 3 to 4 times daily. Children under the age of 12: Do not use, consult a doctor.

Other Information: Store under normal storage conditions. Store away from children.

INACTIVE INGREDIENT

Inactive Ingredients: Peppermint leaf oil (Mentha piperita), Eucalyptus globus leaf oil, Dimethyl sulfone (MSM), Boswellia Carterii Extract, Ilex Paraguariensis (Mate) leaf extract, Glucosamine sulfate, Chondroitin sulfte, Magnesium chloride, Tocopherol (natural Vitamin E), Thymol crystals (5-methyl-2-(1-methylethyl)phenol), Water, Ethanol, Glycerin, UREA, Hydroxypropyl methylcellulose.